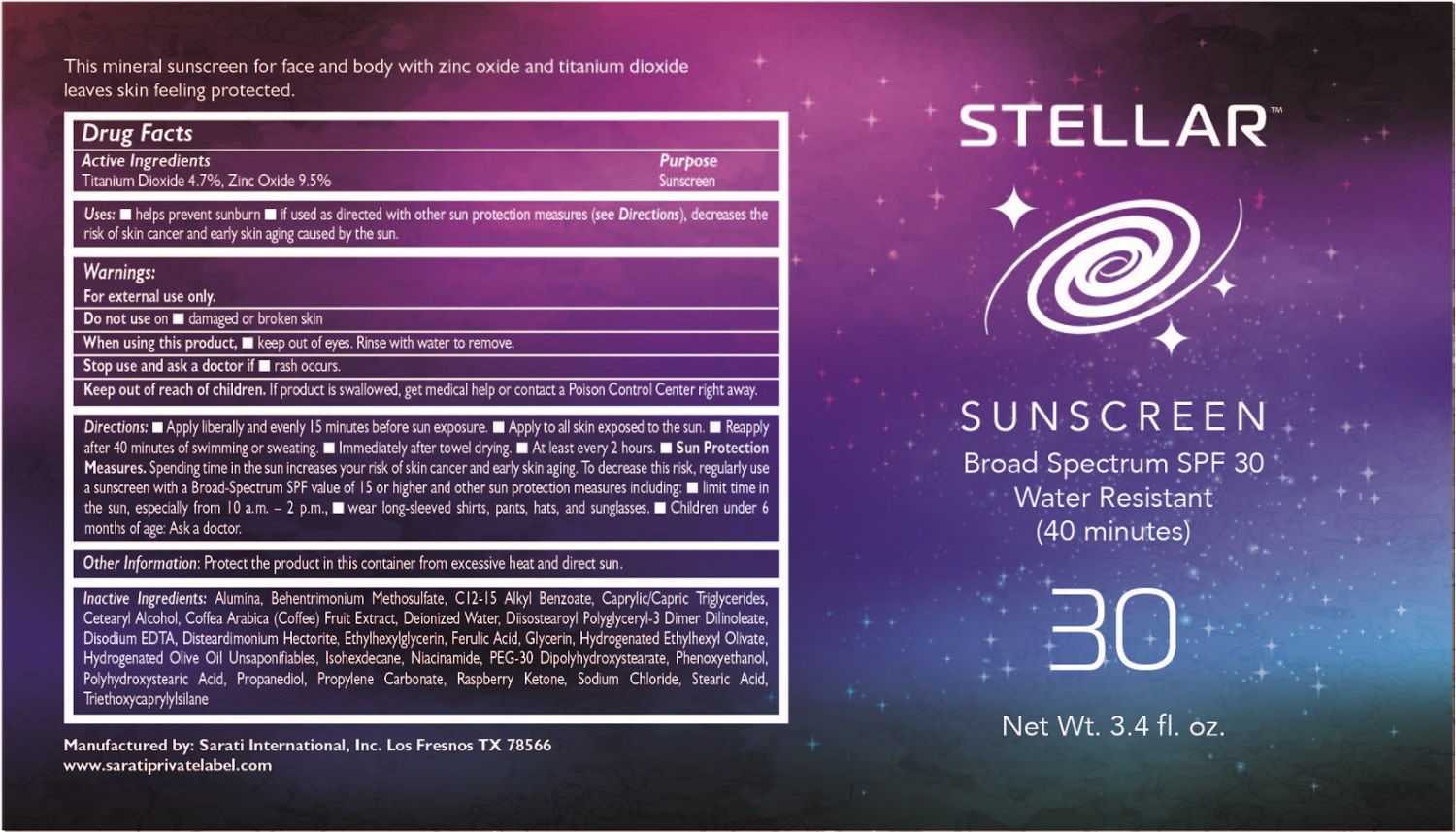 DRUG LABEL: Natural Mineral Sunscreen
NDC: 67676-009 | Form: LOTION
Manufacturer: Sarati International, Inc.
Category: otc | Type: HUMAN OTC DRUG LABEL
Date: 20240425

ACTIVE INGREDIENTS: TITANIUM DIOXIDE 4.95 g/100 g; ZINC OXIDE 9.5 g/100 g
INACTIVE INGREDIENTS: ALUMINUM OXIDE; BEHENTRIMONIUM METHOSULFATE; ALKYL (C12-15) BENZOATE; MEDIUM-CHAIN TRIGLYCERIDES; CETOSTEARYL ALCOHOL; ARABICA COFFEE BEAN; WATER; DIISOSTEAROYL POLYGLYCERYL-3 DIMER DILINOLEATE; PROPYLENE CARBONATE; TRIETHOXYCAPRYLYLSILANE; EDETATE DISODIUM; DISTEARDIMONIUM HECTORITE; ETHYLHEXYLGLYCERIN; FERULIC ACID; GLYCERIN; SODIUM CHLORIDE; 4-(P-HYDROXYPHENYL)-2-BUTANONE; STEARIC ACID; HYDROGENATED ETHYLHEXYL OLIVATE; HYDROGENATED OLIVE OIL UNSAPONIFIABLES; ISOHEXADECANE; NIACINAMIDE; PEG-30 DIPOLYHYDROXYSTEARATE; PHENOXYETHANOL; POLYHYDROXYSTEARIC ACID (2300 MW); PROPANEDIOL

Active Ingredients

Titanium Dioxide 4.7%

Zinc Oxide 9.5%

Purpose

Sunscreen

Uses:

- Helps prevent sunburn
- If used as directed with other sun protection measures (see Directions), decreases the risk of skin cancer and early skin aging caused by the sun

Warnings:

- For external use only

Keep out of reach of children.

If product is swallowed, get medical help or contact a Poison Control Center right away

Directions:

- Apply liberally and evenly 15 minutes before sun exposure. Apply to all skin exposed to the sun.
- Reapply
- after 40 minutes of swimming or sweating
- immediately after towel drying
- at least every 2 hours
- Sun Protection Measures. Spending time in the sun increases your risk of skin cancer and early skin aging. To decrease this risk, regularly use a sunscreen with a Broad-Spectrum SPF value of 15 or higher and other sun protection measures including:
- limit time in the sun, especially from 10 a.m. – 2 p.m.
- wear long-sleeved shirts, pants, hats, and sunglasses.
- Children under 6 months of age: Ask a doctor.

INACTIVE INGREDIENT

Alumina, Behentrimonium Methosulfate, C12-15 Alkyl Benzoate, Caprylic/Capric Triglycerides, Cetearyl Alcohol, Coffea Arabica (Coffee) Fruit Extract, Deionized Water, Diisostearoyl Polyglyceryl-3 Dimer Dilinoleate, Disodium EDTA, Disteardimonium Hectorite, Ethylhexylglycerin, Ferulic Acid, Glycerin, Hydrogenated Ethylhexyl Olivate, Hydrogenated Olive Oil Unsaponifiables, Isohexdecane, Niacinamide, PEG-30 Dipolyhydroxystearate, Phenoxyethanol, Polyhydroxystearic Acid, Propanediol, Propylene Carbonate, Raspberry Ketone, Sodium Chloride, Stearic Acid, Triethoxycaprylylsilane

Other information: Protect the product in this container from excessive heat and direct sun.

RECENT MAJOR CHANGES

Updated directions as required for Broad Spectrum and Water Resistant Testing

Updated label and principal display panel.

Do not use

- on danaged or broken skin

When using this product,

- keep out of eyes. Rinse with water to remove.

Stop use and ask a doctor

- if rash occurs.

PACKAGE LABEL

STELLAR

SUNSCREEN

Broad Spectrum SPF 30

Water Resistant

(40 minutes)

30

Net Wt. 3.4 fl. oz.